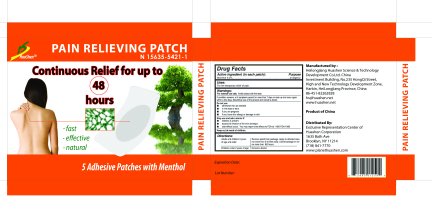 DRUG LABEL: Pain Relieving Patch
NDC: 50309-777 | Form: PATCH
Manufacturer: Heilongjiang Huashen Science & Technology Development Co Ltd 
Category: otc | Type: HUMAN OTC DRUG LABEL
Date: 20100108

ACTIVE INGREDIENTS: MENTHOL 0.2 1/1 1

Pain Relieving Patch

Active Ingredient (in each patch) Purpose

Menthol 0.2 percent Analgesic

Uses:
For the temporary relief of pain.

Warnings:

For external use only. Avoid contact with the eyes.

If condition worsens, or if symptoms persist for more than 7 days or clear up and occur again

within a few days, discontinue use of this product and consult a doctor.

Do not use

- otherwise than as directed

- in the eyes or ears

- if you are pregnant

- if you have skin allergy or damage to skin

Stop use and ask a doctor if

- redness is present

- excessive irritation of the skin develops

- side effects occur. You may report side effects to FDA at 1-800-FDA-1088

Keep out of reach of children.

Directions:

Adults and children 2 years of age and older: Remove patch from package. Apply to affected area not more than 3-4 times daily. Leave bandage

on for no more than 48 hours.

Children under 2 years of age: Consult a doctor.

DESCRIPTION

Manufactured by:

Heilongjiang Huashen Science and Technology

Development Co. Ltd. China

Investment Building, No.235 HongQi Street,

High and New Technology Development Zone,

Harbin, HeilLongjiang Province, China

86 451 82262828

hs huashen.net

www.huashen.net

Product of China

Distributed By:

Exclusive Representation Center of

Huashen Corporation

1635 Bath Ave

Brooklyn, NY 11214

718 841 7770

www planethuashen com

PACKAGE LABEL

HuaShen Pain Relieving Patch

Continuous Relief for up to

48

hours

- fast

- effective

- natural

5 Adhesive Patches with Menthol